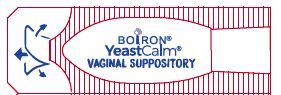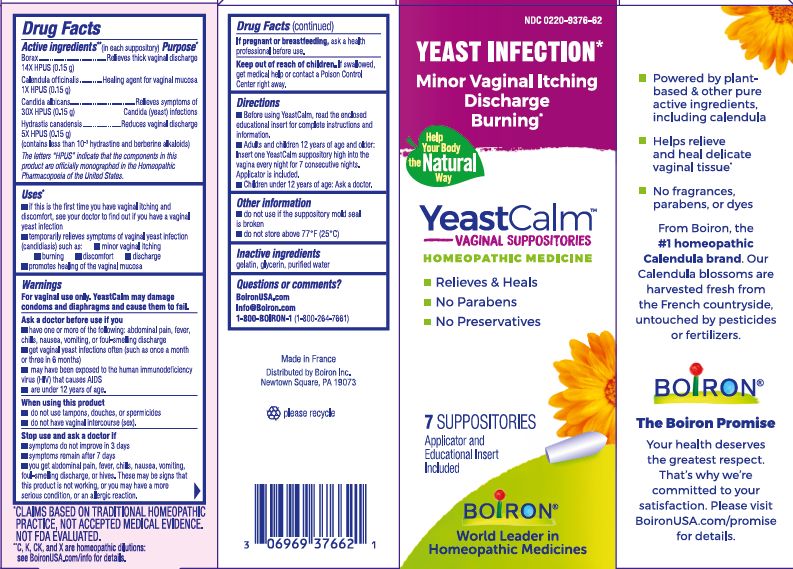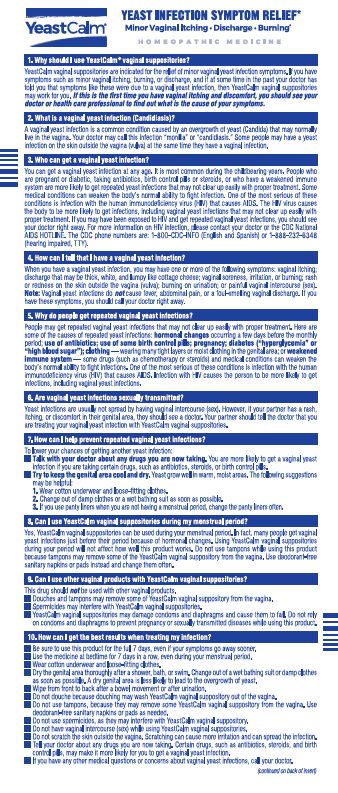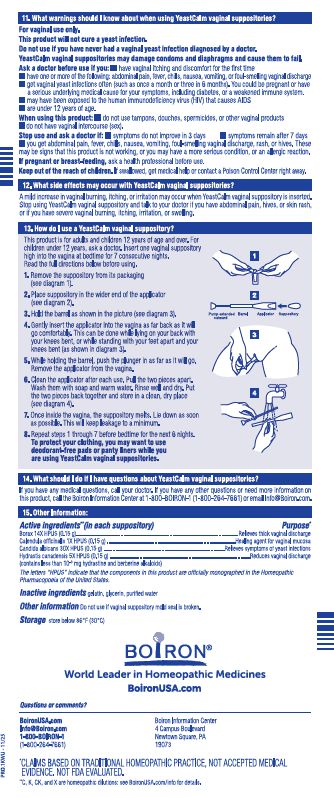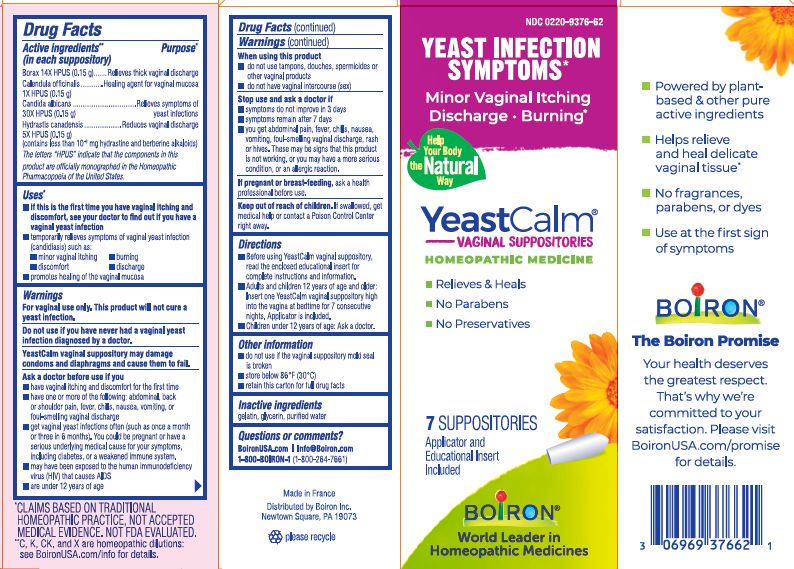 DRUG LABEL: YeastCalm
NDC: 0220-9376 | Form: SUPPOSITORY
Manufacturer: Laboratoires Boirdon
Category: homeopathic | Type: HUMAN OTC DRUG LABEL
Date: 20260109

ACTIVE INGREDIENTS: GOLDENSEAL 5 [hp_X]/1 1; CALENDULA OFFICINALIS FLOWERING TOP 1 [hp_X]/1 1; SODIUM BORATE 14 [hp_X]/1 1; CANDIDA ALBICANS 30 [hp_X]/1 1
INACTIVE INGREDIENTS: WATER; GELATIN; GLYCERIN

YeastCalm

Active Ingredients** (in each suppository)

Borax 14X HPUS (0.15 g)

Calendula officinalis 1X HPUS (0.15 g)

Candida albicans 30X HPUS (0.15 g)

Hydrastis canadensis 5X HPUS (0.15 g) (contains less than 10^-3 hydrastine and berberine alkaloids)

The letters "HPUS" indicate that the components in the product are officially monographed in the Homeopathic Pharmacopoeia of the United States.

Purpose*

Borax 14X HPUS (0.15 g) ... Relieves thick vaginal discharge

Calendula officinalis 1X HPUS (0.15 g) ... Healing agent for vaginal mucosa

Candida albicans 30X HPUS (0.15 g) ... Relieves symptoms of yeast infections

Hydrastis canadensis 5X HPUS (0.15 g) ... Reduces vaginal discharge

Uses*

- if this is the first time you have vaginal itching and discomfort, see your doctor to find out if you have a vaginal yeast infection
- temporarily relieves symptoms of vaginal yeast infection (candidiasis) such as:

- minor vaginal itching
- burning
- discomfort
- discharge
- promotes healing of the vaginal mucosa

WARNINGS

For vaginal use only. This product will not cure a yeast infection.

Do not use if you have never had a vaginal yeast infection diagnosed by a doctor.

YeastCalm vaginal suppository may damage condoms and diaphragms and cause them to fail.

Ask a doctor before use if you

- have vaginal itching and discomfort for the first time
- have one or more of the following: abdominal, back or shoulder pain, fever, chills, nausea, vomiting, or foul-smelling discharge
- get vaginal yeast infections often (such as once a month or three in 6 months). You could be pregnant or have a serious underlying medical cause for your symptoms, including diabetes, or a weakened immune system.
- may have been exposed to the human immunodeficiency virus (HIV) that causes AIDS
- are under 12 years of age.

When using this product

- do not use tampons, douches, spermicides or other vaginal products
- do not have vaginal intercourse (sex)

Stop use and ask a doctor if

- symptoms do not improve in 3 days
- symptoms remain after 7 days
- you get abdominal pain, fever, chills, nausea, vomiting, foul-smelling vaginal discharge, or hives. These may be signs that this product is not working, or you may have a more serious condition, or allergic reaction.

PREGNANCY OR BREAST FEEDING

If pregnant or breast-feeding, ask a health professional before use.

Keep out of reach of children. If swallowed, get medical help or contact a Poison Control Center right away.

Directions

- Before using YeastCalm vaginal suppository, read the enclosed educational insert for complete instructions and information.
- Adults 12 years of age and older: Insert one YeastCalm vaginal suppository high into the vagina at bedtime for 7 consecutive nights. Applicator is included.
- Children under 12 years of age: Ask a doctor.

INACTIVE INGREDIENT

gelatin, glycerin, purified water

QUESTIONS

BoironUSA.com

Info@Boiron.com

1-800-BOIRON-1 (1-800-264-7661)

Made in France

Distributed by Boiron Inc.

Newtown Square, PA 19073

- do not use if the suppository mold seal is broken
- do not store above 86° F (30° C)
- retain this carton for full drug facts

Yeast Infection Symptoms*

Minor Vaginal Itching Discharge Burning*

7 Suppositories

Applicator and educational insert included

*CLAIMS BASED ON TRADITIONAL HOMEOPATHIC PRACTICE NOT ACCEPTED MEDICAL EVIDENCE. NOT FDA EVALUATED.
**C,K,CK, and X are homeopathic dilutions: see BoironUSA.com/info for details.